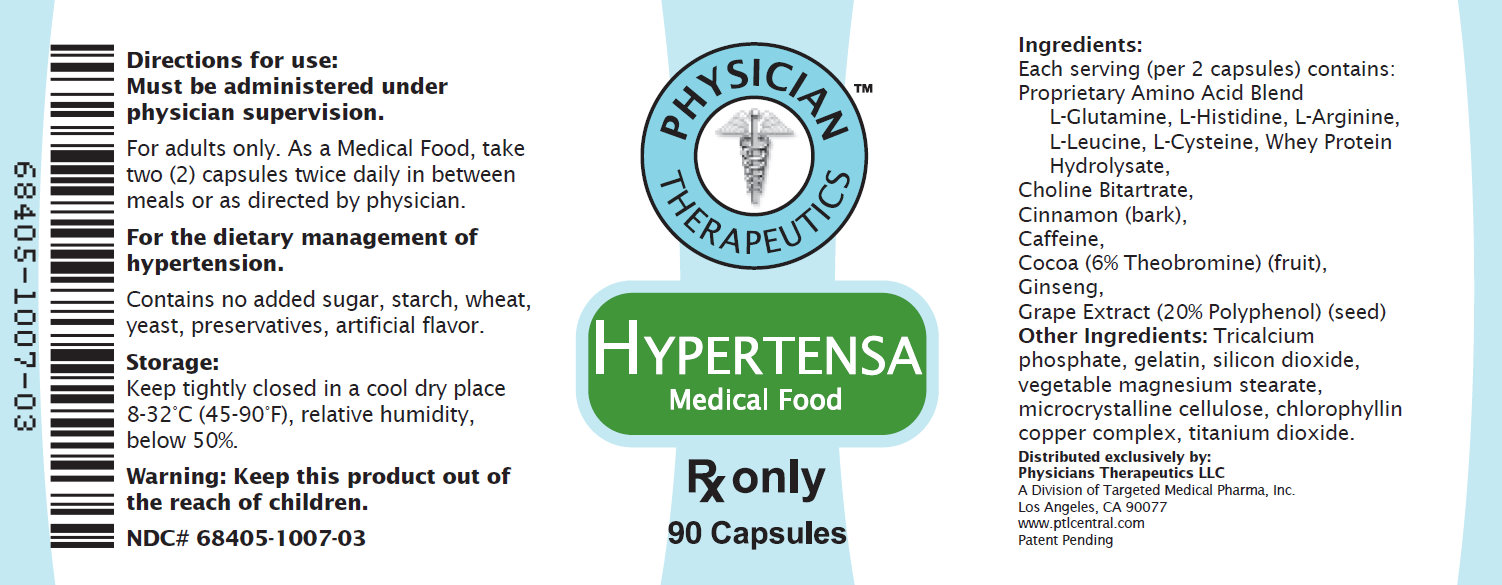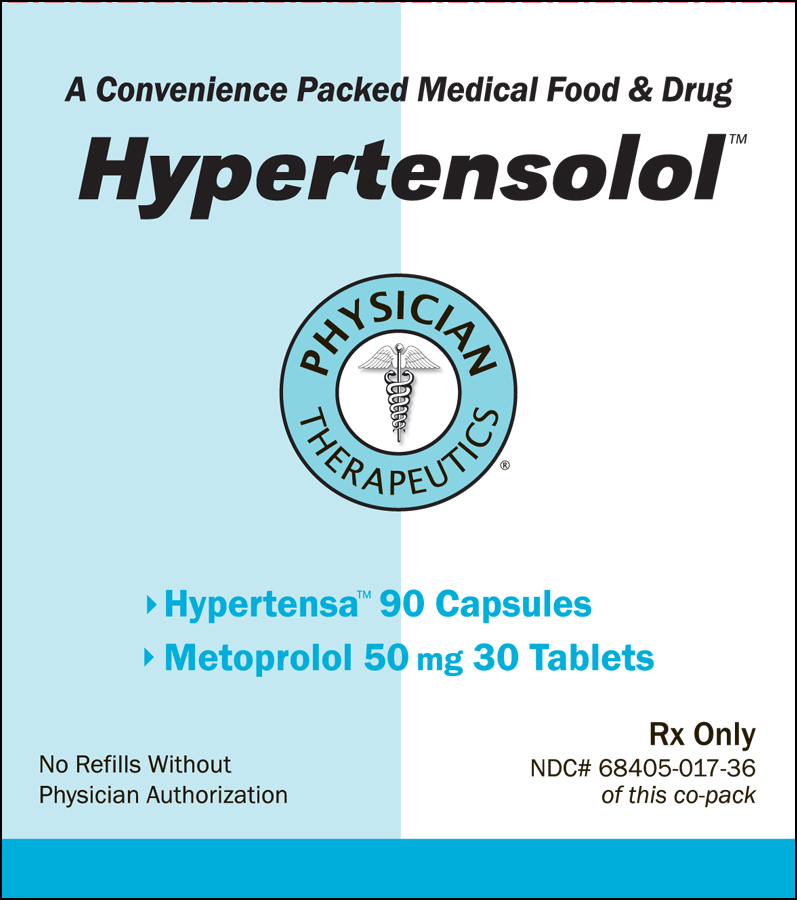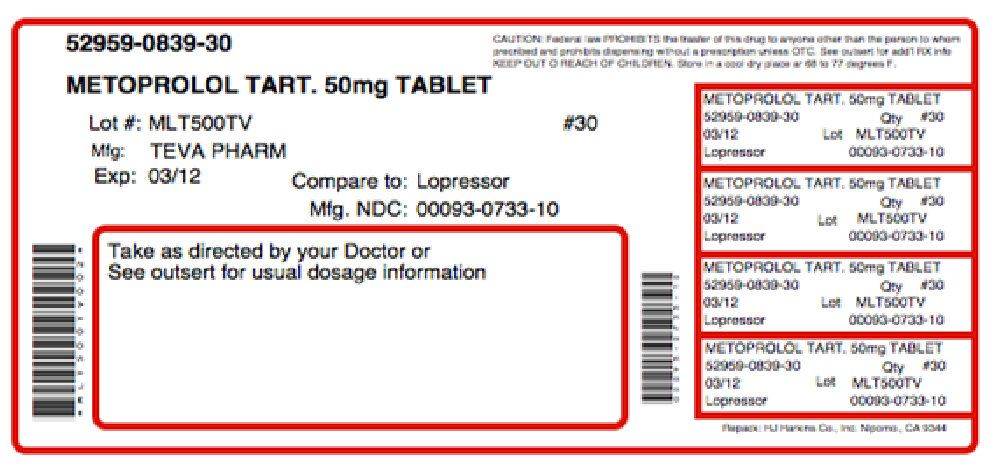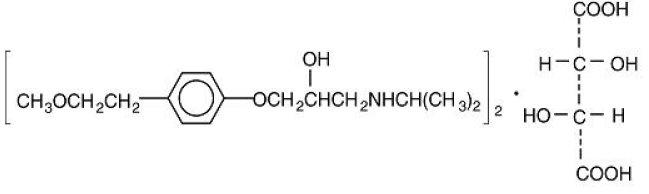 DRUG LABEL: Hypertensolol
NDC: 68405-017 | Form: KIT | Route: ORAL
Manufacturer: Physician Therapeutics LLC
Category: prescription | Type: HUMAN PRESCRIPTION DRUG LABEL
Date: 20110801

ACTIVE INGREDIENTS: METOPROLOL TARTRATE 50 mg/1 1; ARGININE 90 mg/1 1
INACTIVE INGREDIENTS: SILICON DIOXIDE; HYPROMELLOSES; LACTOSE MONOHYDRATE; MAGNESIUM STEARATE; POLYETHYLENE GLYCOL; POVIDONE; PROPYLENE GLYCOL; SODIUM STARCH GLYCOLATE TYPE A POTATO; TALC; TITANIUM DIOXIDE; D&C RED NO. 30; ALUMINUM OXIDE; MAGNESIUM STEARATE; CELLULOSE, MICROCRYSTALLINE; MALTODEXTRIN; GELATIN

Hypertensolol

DESCRIPTION

Metoprolol tartrate is a selective beta1-adrenoreceptor blocking agent, available as 50 and 100 mg tablets for oral administration. Metoprolol tartrate is 1-(isopropylamino)-3-[p-(2-methoxyethyl) phenoxy]-2-propanol (2:1) dextro-tartrate salt, and its structural formula is:

(C15H25NO3)2-C4H6O6 M.W. 684.82Metoprolol tartrate is a white, practically odorless, crystalline powder. It is very soluble in water; freely soluble in methylene chloride,in chloroform, and in alcohol; slightly soluble in acetone; and insoluble in ether.Metoprolol tartrate tablets USP, for oral administration, are available as tablets containing 50 mg or 100 mg of metoprolol tartrate. Inaddition each tablet contains the inactive ingredients: colloidal silicon dioxide, hypromellose, lactose (hydrous), magnesium stearate,polyethylene glycol, povidone, propylene glycol, sodium starch glycolate, talc, titanium dioxide; and in the 50 mg tablets DandC RedNo. 30 aluminum lake and in the 100 mg tablets FDandC Blue No. 1 aluminum lake and FDandC Blue No. 2 aluminum lake.

CLINICAL PHARMACOLOGY
Metoprolol tartrate is a beta-adrenergic receptor blocking agent. In vitro and in vivo animal studies have shown that it has a preferential effect on beta1 adrenoreceptors, chiefly located in cardiac muscle. This preferential effect is not absolute, however, and at higher doses, metoprolol tartrate also inhibits beta2 adrenoreceptors, chiefly located in the bronchial and vascular musculature.
Clinical pharmacology studies have confirmed the beta-blocking activity of metoprolol in man, as shown by (1) reduction in heart rate and cardiac output at rest and upon exercise, (2) reduction of systolic blood pressure upon exercise, (3) inhibition of isoproterenol-induced tachycardia, and (4) reduction of reflex orthostatic tachycardia.
Relative beta1 selectivity has been confirmed by the following: (1) In normal subjects, metoprolol is unable to reverse the beta2-mediated vasodilating effects of epinephrine. This contrasts with the effect of nonselective (beta1 plus beta2) beta blockers, which completely reverse the vasodilating effects of epinephrine. (2) In asthmatic patients, metoprolol reduces FEV1 and FVC significantly less than a nonselective beta blocker, propranolol, at equivalent beta1-receptor blocking doses.
Metoprolol has no intrinsic sympathomimetic activity, and membrane-stabilizing activity is detectable only at doses much greater than required for beta blockade. Metoprolol crosses the blood-brain barrier and has been reported in the CSF in a concentration 78% of the simultaneous plasma concentration. Animal and human experiments indicate that metoprolol slows the sinus rate and decreases AV nodal conduction.
In controlled clinical studies, metoprolol tartrate has been shown to be an effective antihypertensive agent when used alone or as concomitant therapy with thiazide-type diuretics, at dosages of 100 to 450 mg daily. In controlled, comparative, clinical studies, metoprolol has been shown to be as effective an antihypertensive agent as propranolol, methyldopa, and thiazide-type diuretics, and to be equally effective in supine and standing positions.
The mechanism of the antihypertensive effects of beta-blocking agents has not been elucidated. However, several possible mechanisms have been proposed: (1) competitive antagonism of catecholamines at peripheral (especially cardiac) adrenergic neuron sites, leading to decreased cardiac output; (2) a central effect leading to reduced sympathetic outflow to the periphery; and (3) suppression of renin activity.
By blocking catecholamine-induced increases in heart rate, in velocity and extent of myocardial contraction, and in blood pressure, metoprolol reduces the oxygen requirements of the heart at any given level of effort, thus making it useful in the long-term management of angina pectoris. However, in patients with heart failure, beta-adrenergic blockade may increase oxygen requirements by increasing left ventricular fiber length and end-diastolic pressure.
Although beta-adrenergic receptor blockade is useful in the treatment of angina and hypertension, there are situations in which sympathetic stimulation is vital. In patients with severely damaged hearts, adequate ventricular function may depend on sympathetic drive. In the presence of AV block, beta blockade may prevent the necessary facilitating effect of sympathetic activity on conduction. Beta2-adrenergic blockade results in passive bronchial constriction by interfering with endogenous adrenergic bronchodilator activity in patients subject to bronchospasm and may also interfere with exogenous bronchodilators in such patients.
In controlled clinical trials, metoprolol tartrate, administered two or four times daily, has been shown to be an effective antianginal agent, reducing the number of angina attacks and increasing exercise tolerance. The dosage used in these studies ranged from 100 to 400 mg daily. A controlled, comparative, clinical trial showed that metoprolol was indistinguishable from propranolol in the treatment of angina pectoris.
In a large (1,395 patients randomized), double-blind, placebo-controlled clinical study, metoprolol was shown to reduce 3 month mortality by 36% in patients with suspected or definite myocardial infarction.
Patients were randomized and treated as soon as possible after their arrival in the hospital, once their clinical condition had stabilized and their hemodynamic status had been carefully evaluated. Subjects were ineligible if they had hypotension, bradycardia, peripheral signs of shock, and/or more than minimal basal rales as signs of congestive heart failure. Initial treatment consisted of intravenous followed by oral administration of metoprolol tartrate or placebo, given in a coronary care or comparable unit. Oral maintenance therapy with metoprolol or placebo was then continued for 3 months. After this double-blind period, all patients were given metoprolol tartrate and followed up to 1 year.
The median delay from the onset of symptoms to the initiation of therapy was 8 hours in both the metoprolol- and placebo-treatment groups. Among patients treated with metoprolol, there were comparable reductions in 3 month mortality for those treated early (≤ 8 hours) and those in whom treatment was started later. Significant reductions in the incidence of ventricular fibrillation and in chest pain following initial intravenous therapy were also observed with metoprolol and were independent of the interval between onset of symptoms and initiation of therapy.
The precise mechanism of action of metoprolol in patients with suspected or definite myocardial infarction is not known.
In this study, patients treated with metoprolol received the drug both very early (intra-venously) and during a subsequent 3 month period, while placebo patients received no beta-blocker treatment for this period. The study thus was able to show a benefit from the overall metoprolol regimen but cannot separate the benefit of very early intravenous treatment from the benefit of later beta-blocker therapy. Nonetheless, because the overall regimen showed a clear beneficial effect on survival without evidence of an early adverse effect on survival, one acceptable dosage regimen is the precise regimen used in the trial. Because the specific benefit of very early treatment remains to be defined however, it is also reasonable to administer the drug orally to patients at a later time as is recommended for certain other beta blockers.

Pharmacokinetics
In man, absorption of metoprolol is rapid and complete. Plasma levels following oral administration, however, approximate 50% of levels following intravenous administration, indicating about 50% first-pass metabolism.
Plasma levels achieved are highly variable after oral administration. Only a small fraction of the drug (about 12%) is bound to human serum albumin. Metoprolol is a racemic mixture of R- and S-enantiomers. Less than 5% of an oral dose of metoprolol is recovered unchanged in the urine; the rest is excreted by the kidneys as metabolites that appear to have no clinical significance. The systemic availability and half-life of metoprolol in patients with renal failure do not differ to a clinically significant degree from those in normal subjects. Consequently, no reduction in dosage is usually needed in patients with chronic renal failure.
Metoprolol is extensively metabolized by the cytochrome P450 enzyme system in the liver. The oxidative metabolism of metoprolol is under genetic control with a major contribution of the polymorphic cytochrome P450 isoform 2D6 (CYP2D6). There are marked ethnic differences in the prevalence of the poor metabolizers (PM) phenotype. Approximately 7% of Caucasians and less than 1% Asian are poor metabolizers.
Poor CYP2D6 metabolizers exhibit several-fold higher plasma concentrations of metoprolol than extensive metabolizers with normal CYP2D6 activity. The elimination half-life of metoprolol is about 7.5 hours in poor metabolizers and 2.8 hours in extensive metabolizers. However, the CYP2D6 dependent metabolism of metoprolol seems to have little or no effect on safety or tolerability of the drug. None of the metabolites of metoprolol contribute significantly to its beta-blocking effect.
Significant beta-blocking effect (as measured by reduction of exercise heart rate) occurs within 1 hour after oral administration, and its duration is dose-related. For example, a 50% reduction of the maximum registered effect after single oral doses of 20, 50, and 100 mg occurred at 3.3, 5.0, and 6.4 hours, respectively, in normal subjects. After repeated oral dosages of 100 mg twice daily, a significant reduction in exercise systolic blood pressure was evident at 12 hours.
Following intravenous administration of metoprolol, the urinary recovery of unchanged drug is approximately 10%. When the drug was infused over a 10 minute period, in normal volunteers, maximum beta blockade was achieved at approximately 20 minutes. Doses of 5 mg and 15 mg yielded a maximal reduction in exercise-induced heart rate of approximately 10% and 15%, respectively. The effect on exercise heart rate decreased linearly with time at the same rate for both doses, and disappeared at approximately 5 hours and 8 hours for the 5 mg and 15 mg doses, respectively.
Equivalent maximal beta-blocking effect is achieved with oral and intravenous doses in the ratio of approximately 2.5:1.
There is a linear relationship between the log of plasma levels and reduction of exercise heart rate. However, antihypertensive activity does not appear to be related to plasma levels. Because of variable plasma levels attained with a given dose and lack of a consistent relationship of antihypertensive activity to dose, selection of proper dosage requires individual titration.
In several studies of patients with acute myocardial infarction, intravenous followed by oral administration of metoprolol caused a reduction in heart rate, systolic blood pressure, and cardiac output. Stroke volume, diastolic blood pressure, and pulmonary artery end diastolic pressure remained unchanged.
In patients with angina pectoris, plasma concentration measured at 1 hour is linearly related to the oral dose within the range of 50 to 400 mg. Exercise heart rate and systolic blood pressure are reduced in relation to the logarithm of the oral dose of metoprolol. The increase in exercise capacity and the reduction in left ventricular ischemia are also significantly related to the logarithm of the oral dose.
In elderly subjects with clinically normal renal and hepatic function, there are no significant differences in metoprolol pharmacokinetics compared to young subjects.

INDICATIONS AND USAGE
Hypertension
Metoprolol tartrate tablets are indicated for the treatment of hypertension. They may be used alone or in combination with other antihypertensive agents.
Angina Pectoris
Metoprolol tartrate tablets are indicated in the long-term treatment of angina pectoris.
Myocardial Infarction
Metoprolol tartrate tablets are indicated in the treatment of hemodynamically stable patients with definite or suspected acute myocardial infarction to reduce cardiovascular mortality. Treatment with intravenous metoprolol tartrate can be initiated as soon as the patient's clinical condition allows (see DOSAGE AND ADMINISTRATION, CONTRAINDICATIONS, and WARNINGS). Alternatively, treatment can begin within 3 to 10 days of the acute event (see DOSAGE AND ADMINISTRATION).

CONTRAINDICATIONS
Hypertension and Angina
Metoprolol tartrate is contraindicated in sinus bradycardia, heart block greater than first degree, cardiogenic shock, and overt cardiac failure (see WARNINGS).
Hypersensitivity to metoprolol and related derivatives, or to any of the excipients; hypersensitivity to other beta blockers (cross sensitivity between beta blockers can occur).
Sick-sinus syndrome.
Severe peripheral arterial circulatory disorders.
Myocardial Infarction
Metoprolol is contraindicated in patients with a heart rate less than 45 beats/min; second- and third-degree heart block; significant first-degree heart block (P-R interval greater than or equal to 0.24 sec); systolic blood pressure less than 100 mmHg; or moderate-to-severe cardiac failure (see WARNINGS).

WARNINGS
Hypertension and Angina
Cardiac Failure
Sympathetic stimulation is a vital component supporting circulatory function in congestive heart failure, and beta blockade carries the potential hazard of further depressing myocardial contractility and precipitating more severe failure. In hypertensive and angina patients who have congestive heart failure controlled by digitalis and diuretics, metoprolol should be administered cautiously.
In Patients Without a History of Cardiac Failure
Continued depression of the myocardium with beta-blocking agents over a period of time can, in some cases, lead to cardiac failure. At the first sign or symptom of impending cardiac failure, patients should be fully digitalized and/or given a diuretic. The response should be observed closely. If cardiac failure continues, despite adequate digitalization and diuretic therapy, metoprolol should be withdrawn.

Bronchospastic Diseases
PATIENTS WITH BRONCHOSPASTIC DISEASES SHOULD, IN GENERAL, NOT RECEIVE BETA BLOCKERS, including metoprolol. Because of its relative beta1 selectivity, however, metoprolol may be used with caution in patients with bronchospastic disease who do not respond to, or cannot tolerate, other antihypertensive treatment. Since beta1 selectivity is not absolute, a beta2-stimulating agent should be administered concomitantly, and the lowest possible dose of metoprolol tartrate should be used. In these circumstances it would be prudent initially to administer metoprolol in smaller doses three times daily, instead of larger doses two times daily, to avoid the higher plasma levels associated with the longer dosing interval (see DOSAGE AND ADMINISTRATION).
Major Surgery
The necessity or desirability of withdrawing beta-blocking therapy, including metoprolol, prior to major surgery is controversial; the impaired ability of the heart to respond to reflex adrenergic stimuli may augment the risks of general anesthesia and surgical procedures.
Metoprolol, like other beta blockers, is a competitive inhibitor of beta-receptor agonists, and its effects can be reversed by administration of such agents, e.g., dobutamine or isoproterenol. However, such patients may be subject to protracted severe hypotension. Difficulty in restarting and maintaining the heart beat has also been reported with beta blockers.
Diabetes and Hypoglycemia
Metoprolol should be used with caution in diabetic patients if a beta-blocking agent is required. Beta blockers may mask tachycardia occurring with hypoglycemia, but other manifestations such as dizziness and sweating may not be significantly affected.
Pheochromocytoma
If metoprolol is used in the setting of pheochromocytoma, it should be given in combination with an alpha blocker, and only after the alpha blocker has been initiated. Administration of beta blockers alone in the setting of pheochromocytoma has been associated with a paradoxical increase in blood pressure due to the attenuation of beta-mediated vasodilatation in skeletal muscle.
Thyrotoxicosis
Beta-adrenergic blockade may mask certain clinical signs (e.g., tachycardia) of hyperthyroidism. Patients suspected of developing thyrotoxicosis should be managed carefully to avoid abrupt withdrawal of beta blockade, which might precipitate a thyroid storm.
Myocardial Infarction
Cardiac Failure
Sympathetic stimulation is a vital component supporting circulatory function, and beta blockade carries the potential hazard of depressing myocardial contractility and precipitating or exacerbating minimal cardiac failure.
During treatment with metoprolol, the hemodynamic status of the patient should be carefully monitored. If heart failure occurs or persists despite appropriate treatment, metoprolol should be discontinued.
Bradycardia
Metoprolol produces a decrease in sinus heart rate in most patients; this decrease is greatest among patients with high initial heart rates and least among patients with low initial heart rates. Acute myocardial infarction (particularly inferior infarction) may in itself produce significant lowering of the sinus rate. If the sinus rate decreases to less than 40 beats/min, particularly if associated with evidence of lowered cardiac output, atropine (0.25 to 0.5 mg) should be administered intravenously. If treatment with atropine is not successful, metoprolol should be discontinued, and cautious administration of isoproterenol or installation of a cardiac pacemaker should be considered.
AV Block
Metoprolol slows AV conduction and may produce significant first- (P-R interval greater than or equal to 0.26 sec), second-, or third-degree heart block. Acute myocardial infarction also produces heart block.
If heart block occurs, metoprolol should be discontinued and atropine (0.25 to 0.5 mg) should be administered intravenously. If treatment with atropine is not successful, cautious administration of isoproterenol or installation of a cardiac pacemaker should be considered.
Hypotension
If hypotension (systolic blood pressure less than or equal to 90 mmHg) occurs, metoprolol should be discontinued, and the hemodynamic status of the patient and the extent of myocardial damage carefully assessed. Invasive monitoring of central venous, pulmonary capillary wedge, and arterial pressures may be required. Appropriate therapy with fluids, positive inotropic agents, balloon counterpulsation, or other treatment modalities should be instituted. If hypotension is associated with sinus bradycardia or AV block, treatment should be directed at reversing these (see above).
Bronchospastic Diseases
PATIENTS WITH BRONCHOSPASTIC DISEASES SHOULD, IN GENERAL, NOT RECEIVE BETA BLOCKERS, including metoprolol. Because of its relative beta1 selectivity, metoprolol may be used with extreme caution in patients with bronchospastic disease. Because it is unknown to what extent beta2-stimulating agents may exacerbate myocardial ischemia and the extent of infarction, these agents should not be used prophylactically. If bronchospasm not related to congestive heart failure occurs, metoprolol should be discontinued. A theophylline derivative or a beta2 agonist may be administered cautiously, depending on the clinical condition of the patient. Both theophylline derivatives and beta2 agonists may produce serious cardiac arrhythmias.

BOXED WARNING

Ischemic Heart Disease
Following abrupt cessation of therapy with certain beta-blocking agents, exacerbations of angina pectoris and, in some cases, myocardial infarction have occurred. When discontinuing chronically administered metoprolol, particularly in patients with ischemic heart disease, the dosage should be gradually reduced over a period of 1 to 2 weeks and the patient should be carefully monitored. If angina markedly worsens or acute coronary insufficiency develops, metoprolol administration should be reinstated promptly, at least temporarily, and other measures appropriate for the management of unstable angina should be taken. Patients should be warned against interruption or discontinuation of therapy without the physician's advice. Because coronary artery disease is common and may be unrecognized, it may be prudent not to discontinue metoprolol therapy abruptly even in patients treated only for hypertension.

PRECAUTIONS
General
Metoprolol should be used with caution in patients with impaired hepatic function.

Information for Patients
Patients should be advised to take metoprolol regularly and continuously, as directed, with or immediately following meals. If a dose should be missed, the patient should take only the next scheduled dose (without doubling it). Patients should not discontinue metoprolol without consulting the physician.
Patients should be advised (1) to avoid operating automobiles and machinery or engaging in other tasks requiring alertness until the patient's response to therapy with metoprolol has been determined; (2) to contact the physician if any difficulty in breathing occurs; (3) to inform the physician or dentist before any type of surgery that he or she is taking metoprolol.

Drug Interactions
Catecholamine-depleting drugs (e.g., reserpine) may have an additive effect when given with beta-blocking agents. Patients treated with metoprolol plus a catecholamine depletor should therefore be closely observed for evidence of hypotension or marked bradycardia, which may produce vertigo, syncope, or postural hypotension.
Both digitalis glycosides and beta blockers slow atrioventricular conduction and decrease heart rate. Concomitant use can increase the risk of bradycardia.
Risk of Anaphylactic Reaction
While taking beta blockers, patients with a history of severe anaphylactic reaction to a variety of allergens may be more reactive to repeated challenge, either accidental, diagnostic, or therapeutic. Such patients may be unresponsive to the usual doses of epinephrine used to treat allergic reaction.
General Anesthetics
Some inhalation anesthetics may enhance the cardiodepressant effect of beta blockers (see WARNINGS, Major Surgery).
CYP2D6 Inhibitors
Potent inhibitors of the CYP2D6 enzyme may increase the plasma concentration of metoprolol. Strong inhibition of CYP2D6 would mimic the pharmacokinetics of CYP2D6 poor metabolizer (see Pharmacokinetics). Caution should therefore be exercised when coadministering potent CYP2D6 inhibitors with metoprolol. Known clinically significant potent inhibitors of CYP2D6 are antidepressants such as fluoxetine, paroxetine or bupropion, antipsychotics such as thioridazine, antiarrhythmics such as quinidine or propafenone, antiretrovirals such as ritonavir, antihistamines such as diphenhydramine, antimalarials such as hydroxychloroquine or quinidine, antifungals such as terbinafine and medications for stomach ulcers such as cimetidine.
Clonidine
If a patient is treated with clonidine and metoprolol concurrently, and clonidine treatment is to be discontinued, metoprolol should be stopped several days before clonidine is withdrawn. Rebound hypertension that can follow withdrawal of clonidine may be increased in patients receiving concurrent beta-blocker treatment.

Carcinogenesis, Mutagenesis, Impairment of Fertility
Long-term studies in animals have been conducted to evaluate carcinogenic potential. In a 2 year study in rats at three oral dosage levels of up to 800 mg/kg per day, there was no increase in the development of spontaneously occurring benign or malignant neoplasms of any type. The only histologic changes that appeared to be drug related were an increased incidence of generally mild focal accumulation of foamy macrophages in pulmonary alveoli and a slight increase in biliary hyperplasia. In a 21 month study in Swiss albino mice at three oral dosage levels of up to 750 mg/kg per day, benign lung tumors (small adenomas) occurred more frequently in female mice receiving the highest dose than in untreated control animals. There was no increase in malignant or total (benign plus malignant) lung tumors, or in the overall incidence of tumors or malignant tumors. This 21 month study was repeated in CD-1 mice, and no statistically or biologically significant differences were observed between treated and control mice of either sex for any type of tumor.
All mutagenicity tests performed (a dominant lethal study in mice, chromosome studies in somatic cells, a Salmonella/mammalian-microsome mutagenicity test, and a nucleus anomaly test in somatic interphase nuclei) were negative.
No evidence of impaired fertility due to metoprolol was observed in a study performed in rats at doses up to 55.5 times the maximum daily human dose of 450 mg.

Pregnancy Category C
Metoprolol has been shown to increase postimplantation loss and decrease neonatal survival in rats at doses up to 55.5 times the maximum daily human dose of 450 mg. Distribution studies in mice confirm exposure of the fetus when metoprolol is administered to the pregnant animal. These studies have revealed no evidence of impaired fertility or teratogenicity. There are no adequate and well-controlled studies in pregnant women. Because animal reproduction studies are not always predictive of human response, this drug should be used during pregnancy only if clearly needed.

Nursing Mothers
Metoprolol is excreted in breast milk in a very small quantity. An infant consuming 1 liter of breast milk daily would receive a dose of less than 1 mg of the drug. Caution should be exercised when metoprolol is administered to a nursing woman.

Pediatric Use
Safety and effectiveness in pediatric patients have not been established.

Geriatric Use
Clinical trials of metoprolol tartrate in hypertension did not include sufficient numbers of elderly patients to determine whether patients over 65 years of age differ from younger subjects in their response to metoprolol tartrate. Other reported clinical experience in elderly hypertensive patients has not identified any difference in response from younger patients.
In worldwide clinical trials of metoprolol tartrate in myocardial infarction, where approximately 478 patients were over 65 years of age (0 over 75 years of age), no age-related differences in safety and effectiveness were found. Other reported clinical experience in myocardial infarction has not identified differences in response between the elderly and younger patients. However, greater sensitivity of some elderly individuals taking metoprolol tartrate cannot be categorically ruled out. Therefore, in general, it is recommended that dosing proceed with caution in this population.

ADVERSE REACTIONS
Hypertension and Angina
Most adverse effects have been mild and transient.
Central Nervous System
Tiredness and dizziness have occurred in about 10 of 100 patients. Depression has been reported in about 5 of 100 patients. Mental confusion and short-term memory loss have been reported. Headache, nightmares, and insomnia have also been reported.
Cardiovascular
Shortness of breath and bradycardia have occurred in approximately 3 of 100 patients. Cold extremities; arterial insufficiency, usually of the Raynaud type; palpitations; congestive heart failure; peripheral edema; and hypotension have been reported in about 1 of 100 patients. Gangrene in patients with preexisiting severe peripheral circulatory disorders has also been reported very rarely (see CONTRAINDICATIONS, WARNINGS, and PRECAUTIONS).
Respiratory
Wheezing (bronchospasm) and dyspnea have been reported in about 1 of 100 patients (see WARNINGS). Rhinitis has also been reported.
Gastrointestinal
Diarrhea has occurred in about 5 of 100 patients. Nausea, dry mouth, gastric pain, constipation, flatulence, and heartburn have been reported in about 1 of 100 patients. Vomiting was a common occurrence. Postmarketing experience reveals very rare reports of hepatitis, jaundice and non-specific hepatic dysfunction. Isolated cases of transaminase, alkaline phosphatase, and lactic dehydrogenase elevations have also been reported.
Hypersensitive Reactions
Pruritus or rash have occurred in about 5 of 100 patients. Very rarely, photosensitivity and worsening of psoriasis has been reported.
Miscellaneous
Peyronie's disease has been reported in fewer than 1 of 100,000 patients. Musculoskeletal pain, blurred vision, and tinnitus have also been reported.
There have been rare reports of reversible alopecia, agranulocytosis, and dry eyes. Discontinuation of the drug should be considered if any such reaction is not otherwise explicable. There have been very rare reports of weight gain, arthritis, and retroperitoneal fibrosis (relationship to metoprolol has not been definitely established).
The oculomucocutaneous syndrome associated with the beta blocker practolol has not been reported with metoprolol.
Myocardial Infarction
Central Nervous System
Tiredness has been reported in about 1 of 100 patients. Vertigo, sleep disturbances, hallucinations, headache, dizziness, visual disturbances, confusion, and reduced libido have also been reported, but a drug relationship is not clear.
Cardiovascular
In the randomized comparison of metoprolol and placebo described in the CLINICAL PHARMACOLOGY section, the following adverse reactions were reported:

 | Metoprolol | Placebo
Hypotension (systolic BP less than 90 mmHg) | 27.4% | 23.2%
Bradycardia (heart rate less than 40 beats/min) | 15.9% | 6.7%
Second- or third-degree heart block | 4.7% | 4.7%
First-degree heart block (P-R 0.26 sec) | 5.3% | 1.9%
Heart failure | 27.5% | 29.6%

Respiratory
Dyspnea of pulmonary origin has been reported in fewer than 1 of 100 patients.
Gastrointestinal
Nausea and abdominal pain have been reported in fewer than 1 of 100 patients.
Dermatologic
Rash and worsened psoriasis have been reported, but a drug relationship is not clear.
Miscellaneous
Unstable diabetes and claudication have been reported, but a drug relationship is not clear.
Potential Adverse Reactions
A variety of adverse reactions not listed above have been reported with other beta-adrenergic blocking agents and should be considered potential adverse reactions to metoprolol.
Central Nervous System
Reversible mental depression progressing to catatonia; an acute reversible syndrome characterized by disorientation for time and place, short-term memory loss, emotional lability, slightly clouded sensorium, and decreased performance on neuropsychometrics.
Cardiovascular
Intensification of AV block (see CONTRAINDICATIONS).
Hematologic
Agranulocytosis, nonthrombocytopenic purpura, thrombocytopenic purpura.
Hypersensitivity Reactions
Fever combined with aching and sore throat, laryngospasm, and respiratory distress.
Postmarketing Experience
The following adverse reactions have been reported during postapproval use of metoprolol: confusional state, an increase in blood triglycerides and a decrease in High Density Lipoprotein (HDL). Because these reports are from a population of uncertain size and are subject to confounding factors, it is not possible to reliably estimate their frequency.

OVERDOSAGE
Acute Toxicity
Several cases of overdosage have been reported, some leading to death.
Oral LD50's (mg/kg): mice, 1158 to 2460; rats, 3090 to 4670.
Signs and Symptoms
Potential signs and symptoms associated with overdosage with metoprolol are bradycardia, hypotension, bronchospasm, and cardiac failure.
Treatment
There is no specific antidote.
In general, patients with acute or recent myocardial infarction may be more hemodynamically unstable than other patients and should be treated accordingly (see WARNINGS, Myocardial Infarction).
On the basis of the pharmacologic actions of metoprolol, the following general measures should be employed:
Elimination of the Drug
Gastric lavage should be performed.
Bradycardia
Atropine should be administered. If there is no response to vagal blockade, isoproterenol should be administered cautiously.
Hypotension
A vasopressor should be administered, e.g., levarterenol or dopamine.
Bronchospasm
A beta2-stimulating agent and/or a theophylline derivative should be administered.
Cardiac Failure
A digitalis glycoside and diuretic should be administered. In shock resulting from inadequate cardiac contractility, administration of dobutamine, isoproterenol, or glucagon may be considered.

DOSAGE AND ADMINISTRATION
Hypertension
The dosage of metoprolol tartrate tablets USP should be individualized. Metoprolol tartrate tablets should be taken with or immediately following meals.
The usual initial dosage of metoprolol tartrate tablets USP is 100 mg daily in single or divided doses, whether used alone or added to a diuretic. The dosage may be increased at weekly (or longer) intervals until optimum blood pressure reduction is achieved. In general, the maximum effect of any given dosage level will be apparent after 1 week of therapy. The effective dosage range of metoprolol tartrate tablets USP is 100 to 450 mg per day. Dosages above 450 mg per day have not been studied. While once-daily dosing is effective and can maintain a reduction in blood pressure throughout the day, lower doses (especially 100 mg) may not maintain a full effect at the end of the 24 hour period, and larger or more frequent daily doses may be required. This can be evaluated by measuring blood pressure near the end of the dosing interval to determine whether satisfactory control is being maintained throughout the day. Beta1 selectivity diminishes as the dose of metoprolol is increased.
Angina Pectoris
The dosage of metoprolol tartrate tablets USP should be individualized. Metoprolol tartrate tablets should be taken with or immediately following meals.
The usual initial dosage of metoprolol tartrate tablets USP 100 mg daily, given in two divided doses. The dosage may be gradually increased at weekly intervals until optimum clinical response has been obtained or there is pronounced slowing of the heart rate. The effective dosage range of metoprolol tartrate tablets USP is 100 to 400 mg per day. Dosages above 400 mg per day have not been studied. If treatment is to be discontinued, the dosage should be reduced gradually over a period of 1 to 2 weeks (see WARNINGS).
Myocardial Infarction
Early Treatment
During the early phase of definite or suspected acute myocardial infarction, treatment with metoprolol tartrate can be initiated as soon as possible after the patient's arrival in the hospital. Such treatment should be initiated in a coronary care or similar unit immediately after the patient's hemodynamic condition has stabilized.
Treatment in this early phase should begin with the intravenous administration of three bolus injections of 5 mg of metoprolol tartrate each; the injections should be given at approximately 2 minute intervals. During the intravenous administration of metoprolol, blood pressure, heart rate, and electrocardiogram should be carefully monitored.
In patients who tolerate the full intravenous dose (15 mg), metoprolol tartrate tablets USP, 50 mg every 6 hours, should be initiated 15 minutes after the last intravenous dose and continued for 48 hours. Thereafter, patients should receive a maintenance dosage of 100 mg twice daily (see Late Treatment below).
Patients who appear not to tolerate the full intravenous dose should be started on metoprolol tartrate tablets USP either 25 mg or 50 mg every 6 hours (depending on the degree of intolerance) 15 minutes after the last intravenous dose or as soon as their clinical condition allows. In patients with severe intolerance, treatment with metoprolol should be discontinued (see WARNINGS).
Late Treatment
Patients with contraindications to treatment during the early phase of suspected or definite myocardial infarction, patients who appear not to tolerate the full early treatment, and patients in whom the physician wishes to delay therapy for any other reason should be started on metoprolol tartrate tablets USP, 100 mg twice daily, as soon as their clinical condition allows. Therapy should be continued for at least 3 months. Although the efficacy of metoprolol beyond 3 months has not been conclusively established, data from studies with other beta blockers suggest that treatment should be continued for 1 to 3 years.
Note: Parenteral drug products should be inspected visually for particulate matter and discoloration prior to administration, whenever solution and container permit.

HOW SUPPLIED
Metoprolol tartrate tablets, USP are available as:
50 mg tablets - round, biconvex, film-coated, pink, scored tablets, debossed "93"-"733" on the scored side, and plain on the other side. Packaged in bottles of 100 and 1000.
100 mg tablets - round, biconvex, film-coated, mottled-blue, scored tablets, debossed "93"-"734" on the scored side, and plain on the other side. Packaged in bottles of 100 and 1000.

STORAGE AND HANDLING

Store at 20o to 25oC (68o to 77oF) [See USP Controlled Room Temperature].
Protect from moisture.
Dispense contents in a tight, light-resistant container as defined in the USP, with a child-resistant closure (as required).
Manufactured In India By:
EMCURE PHARMACEUTICALS LTD.
Hinjwadi, Pune, India
Manufactured For:
TEVA PHARMACEUTICALS USA
Sellersville, PA 18960
Rev. J 11/2009

PACKAGE LABEL

NDC 0093-0733-10

METOPROLOL TARTRATE Tablets USP

50 mg

Each tablet contains:
metoprolol tartrate, USP 50 mg

R only

1000 TABLETS

TEVN

Usual Dosage: See package insert for full prescribing information.

Store at 20o to 25oC (68o to 77oF) [See USP Controlled Room Temperature].Protect from moisture.

This is a bulk package. Dispense contents in a tight, light-resistant container as defined in the USP, with a child-resistant closure (as required).

KEEP THIS AND ALL MEDICATIONS OUT OF THE REACH OF CHILDREN.

Code No.: MH/DRUGS/PD/149 Rev. D 3/2006

Manufactured In India By:
Emcure Pharmaceuticals LTD.
Hinjwadi, Pune, India

Manufactured For:
TEVA PHARMACEUTICALS USA
Sellersville, PA 18960

LOT:

EXP:

N3 0093-0733-10 9

510270035IN01

Hypertensa™ PRODUCT INFORMATION Hypertensa (U.S. patent pending) capsules by oral administration. A specially formulated Medical Food product, consisting of a proprietary blend of amino acids and polyphenol ingredients in specific proportions, for the dietary management of the metabolic processes associated with hypertension (HT). Must be administered under physician supervision. Medical Foods Medical Food products are often used in hospitals (e.g., for burn victims or kidney dialysis patients) and outside of a hospital setting under a physician’s care (e.g., for PKU, AIDS patients, cardiovascular disease, sleep disorders) for the dietary management of diseases in patients with particular medical or metabolic needs due to their disease or condition. Congress defined "Medical Food" in the Orphan Drug Act and Amendments of 1988 as "a system which is formulated to be consumed or administered enterally [or orally] under the supervision of a physician and which is intended for the specific dietary management f a disease or condition for which distinctive nutritional requirements, based on recognized scientific principles, are established by medical evaluation." Medical Foods are complex formulated products, requiring sophisticated and exacting technology. Hypertensa has been developed, manufactured, and labeled in accordance with both the statutory and the FDA regulatory definition of a Medical Food. Hypertensa must be used while the patient is under the ongoing care of a physician. HYPERTENSION (HT) HT as a Metabolic Deficiency Disease A critical component of the definition of a Medical Food is the requirement for a distinctive nutritional deficiency. FDA scientists have proposed a physiologic definition of a distinctive nutritional deficiency as follows: “the dietary management of patients with specific diseases requires, in some instances, the ability to meet nutritional requirements that differ substantially from the needs of healthy persons. For example, in establishing the recommended dietary allowances f r general, healthy population, the Food and Nutrition Board of the Institute of Medicine National Academy of Sciences, recognized that different or distinctive physiologic requirements may exist for certain persons with "special nutritional needs arising from metabolic disorders, chronic diseases, injuries, premature birth, other medical conditions and drug therapies. Thus, the distinctive nutritional needs associated with a disease reflect the total amount needed by a healthy person to support life or maintain homeostasis, adjusted for the distinctive changes in the nutritional needs of the patient as a result of the effects of the disease process on absorption, metabolism and excretion.” It was also proposed that in patients with certain disease states who respond to nutritional therapies, a physiologic deficiency of the nutrient is assumed to exist. For example, if a patient with hypertension responds to an arginine formulation by decreasing the blood pressure, a deficiency of arginine is assumed to exist. Patients with hypertension are known to have nutritional deficiencies of arginine, choline, flavonoids, and certain antioxidants. Patients with hypertension frequently exhibit reduced plasma levels of arginine and have been shown to respond to oral administration of an arginine formulation. Research has shown that arginine reduced diets result in a fall of circulating arginine. Patients with hypertension have activation of the arginase pathway that diverts arginine from the production of nitric oxide to production of deleterious nitrogen molecules such as peroxynitrite leading to a reduced level of production of nitric oxide for a given arginine blood level. Research has also shown that a genetic predisposition can lead to increased arginine requirements in certain patients with hypertension. Arginine is required to fully potentiate nitric oxide synthesis by the arterioles. A deficiency of arginine leads to reduced nitric oxide production by the arterioles. Low fat diets, frequently used by patients with hypertension, are usually arginine deficient. Flavonoids potentiate the production of nitric oxide by the arterioles thereby reducing blood pressure in hypertensive patients. Low fat diets and diets deficient in flavonoid rich foods result in inadequate arginine and flavonoid concentrations, impeding nitric oxide production in certain patients with hypertension. Provision of arginine, choline, and flavonoids with antioxidants, in the correct proportions can restore the production of beneficial nitric oxide, thereby reducing blood pressure.

DESCRIPTION

PRODUCT DESCRIPTION Primary Ingredients Hypertensa consists of a proprietary blend of amino acids, cocoa, cinnamon and flavonoids in specific proportions. These ingredients fall into the category of Generally Regarded as Safe” (GRAS) as defined by the Food and Drug Administration (FDA) (Sections 201(s) and 409 of the Federal Food, Drug, and Cosmetic Act). A GRAS substance is distinguished from a food additive on the basis of the common knowledge about the safety of the substance for its intended use. The standard for an ingredient to achieve GRAS status requires not only technical demonstration of non-toxicity and safety, but also general recognition of safety through widespread usage and agreement of that safety by experts in the field. Many ingredients have been determined by the U.S. Food and Drug Administration (FDA) to be GRAS, and are listed as such by regulation, in Volume 21 Code of Federal Regulations (CFR) Sections 182, 184, and 186. Amino Acids Amino Acids are the building blocks of proteins. All amino acids are GRAS listed as they have been ingested by humans for thousands of years. The doses of the amino acids in Hypertensa are equivalent to those found in the usual human diet. Patients with hypertension may require an increased amount of certain amino acids that cannot be obtained from normal diet alone. Arginine, for example, is a conditional amino acid. The body can make arginine in the liver, but the liver produced arginine can only be used in the liver itself. Arginine is needed to produce nitric oxide (NO). NO is required to dilate the constricted blood vessels that are the cause of high blood pressure. Patients with hypertension have an increase in the enzyme, arginase that degrades arginine before it can be used to produce NO. Some patients with hypertension have a resistance to the use of arginine that is similar to the mechanism found in insulin resistance that is genetically determined. Patients with hypertension cannot acquire sufficient arginine from the diet without ingesting a prohibitively large amount of calories, particularly calories from protein. . Flavonoids Flavonoids are a group of phytochemical compounds found in all vascular plants including fruits and vegetables. They are a part of a larger class of compounds known as polyphenols. Many of the therapeutic or health benefits of colored fruits and vegetables, cocoa, red wine, and green tea are directly related to their flavonoid content. The specially formulated flavonoids found in Hypertensa cannot be obtained from conventional foods in the necessary proportions to elicit a therapeutic response. Other Ingredients Hypertensa contains the following “inactive” or other ingredients, as fillers, excipients, and colorings: magnesium stearate, microcrystalline cellulose, Maltodextrin NF, gelatin (as the capsule material), Physical Description Hypertensa is a yellow to light brown powder. Hypertensa contains L-Glutamine, L-Histadine, L-Arginine, L-Leucine, L-Cysteine, Whey Protein Hydrolysate, Choline Bitartrate, Cinnamon, Caffeine, Cocoa, Ginseng, and Grape Extract.

CLINICAL PHARMACOLOGY

CLINICAL PHARMACOLOGY Mechanism of Action Hypertensa acts by restoring and maintaining the balance of NO in patients with hypertension. Metabolism The amino acids in Hypertensa are primarily absorbed by the stomach and small intestines. All cells metabolize the amino acids in Hypertensa. Circulating arginine and choline blood levels determine the production of NO and acetylcholine. Excretion Hypertensa is not an inhibitor of cytochrome P450 1A2, 2C9, 2C19, 2D6, or 3A4. These isoenzymes are principally responsible for 95% of all detoxification of drugs, with CYP3A4 being responsible for detoxification of roughly 50% of drugs. Amino acids do not appear to have an effect on drug metabolizing enzymes.

INDICATIONS AND USAGE

INDICATIONS FOR USE Hypertensa is intended for the clinical dietary management of the metabolic processes in patients with hypertension.

CLINICAL STUDIES

CLINICAL EXPERIENCE Administration of Hypertensa has demonstrated significant functional improvements in blood pressure when used for the dietary management of the metabolic processes associated with hypertension. Administration of Hypertensa results in the reduction of blood pressure in hypertensive patients. Hypertensa has no effect on normal blood pressure.

CONTRAINDICATIONS

PRECAUTIONS AND CONTRAINDICATIONS Hypertensa is contraindicated in an extremely small number of patients with hypersensitivity to any of the nutritional components of Hypertensa.

ADVERSE REACTIONS

ADVERSE REACTIONS Oral supplementation with L-arginine at high doses up to 15 grams daily is generally well tolerated. The most commonly reported adverse reactions at higher doses — from 15 to 30 grams daily — are nausea, abdominal cramps, and diarrhea. Some patients may experience these symptoms at lower doses. The total combined amount of amino acids in each Hypertensa capsule does not exceed 400 mg.

DRUG INTERACTIONS

DRUG INTERACTIONS Hypertensa does not directly influence the pharmacokinetics of prescription drugs. Clinical experience has shown that administration of Hypertensa may allow for lowering the dose of co-administered drugs under physician supervision. POST-MARKETING SURVEILLANCE Post-marketing surveillance has shown no serious adverse reactions. Reported cases of mild rash and itching may have been associated with allergies to Hypertensa flavonoid ingredients, including cocoa and chocolate. The reactions were transient in nature and subsided within 24 hours.

OVERDOSAGE

OVERDOSE There is a negligible risk of overdose with Hypertensa as the total dosage of amino acids in a one month supply (90 capsules) is less than 36 grams. Overdose symptoms may include diarrhea, weakness, and nausea

DOSAGE AND ADMINISTRATION Recommended Administration For the dietary management of the metabolic processes associated with hypertension. Take (2) capsules once or twice daily, as directed by physician. As with most amino acid formulations Hypertensa should be taken without food to increase the absorption of key ingredients.

HOW SUPPLIED

How Supplied Hypertensa is supplied in green and white, size 0 capsules in bottles of 60 and 90 capsules. Physician Supervision Hypertensa is a Medical Food product available by prescription only, and must be used while the patient is under ongoing physician supervision. U.S. patent pending. Manufactured by Arizona Nutritional Supplements, Inc. Chandler AZ 85225 Distributed by Physician Therapeutics LLC, Los Angeles, CA 90077. www.ptlcentral.com © Copyright 2003-2006, Physician Therapeutics LLC, all rights reserved NDC: 68405-1007-02 NDC: 68405-1007-03

STORAGE AND HANDLING

Storage Store at room temperature, 59-86OF (15-30OC) Protect from light and moisture. Hypertensa is supplied to physicians in a recyclable plastic bottle with a child-resistant cap.

PACKAGE LABEL

PHYSICIAN THERAPEUTICS HYPERTENSA Medical Food Rx only 90 Capsules Directions for use: Must be administered under physician supervision. For adults only. As a Medical Food, take two (2) capsules four times daily in between meals or as directed by physician. For the dietary management of hypertension. Contains no added sugar, starch, wheat, yeast, preservatives, artifical flavor. Storage: Keep tightly closed in a cool dry place 8-320 C (45-900F), relative humidity, below 50%. Warning: Keep this product out of the reach of children. NDC# 68405-1007-03 Ingredients: Each serving (per 2 capsules) contains: Proprietary Amino Acid Blend L-Glutamine L-Histadine, L-Arginine, L-Leucine, L-Cysteine, Whey Protein Hydrolysate, Choline Bitatarate, Cinnamon (bark), Caffeine, Cocoa(6% Theobromine) (fruit), Ginseng, Grape Extract (20% Polyphenol) (seed) other indgredients: Tricalcium phosphate, gelatin, silicon dioxide, vegetable magnesium stearate, microcrystalline cellulose, chlorophyllin copper complex, titanium dioxide. Distributed exclusive by: A Division of Targeted Medical Pharma, Inc Los Angeles, CA 90077 www.ptlcentral.com Patent Pending

PACKAGE LABEL

For the Dietary Management of Hypertension. Two capsules twice daily or as directed by physician. See product label and insert. Hypertensa Medical Food A Convenience Packed Medical Food And Drug Hypertensolol PHYSICIAN THERAPEUTICS > Hypertensa 90 Capsules > Metoprolol 50 mg 30 Tablets No Refills without Physician Authorization Rx Only NDC#68405-398-36 of this co-pack FRONT VIEW As prescribed by physician. See product label and product information insert. Metoprolol 50 mg Rx Drug 68405-8017-38 BACK VIEW